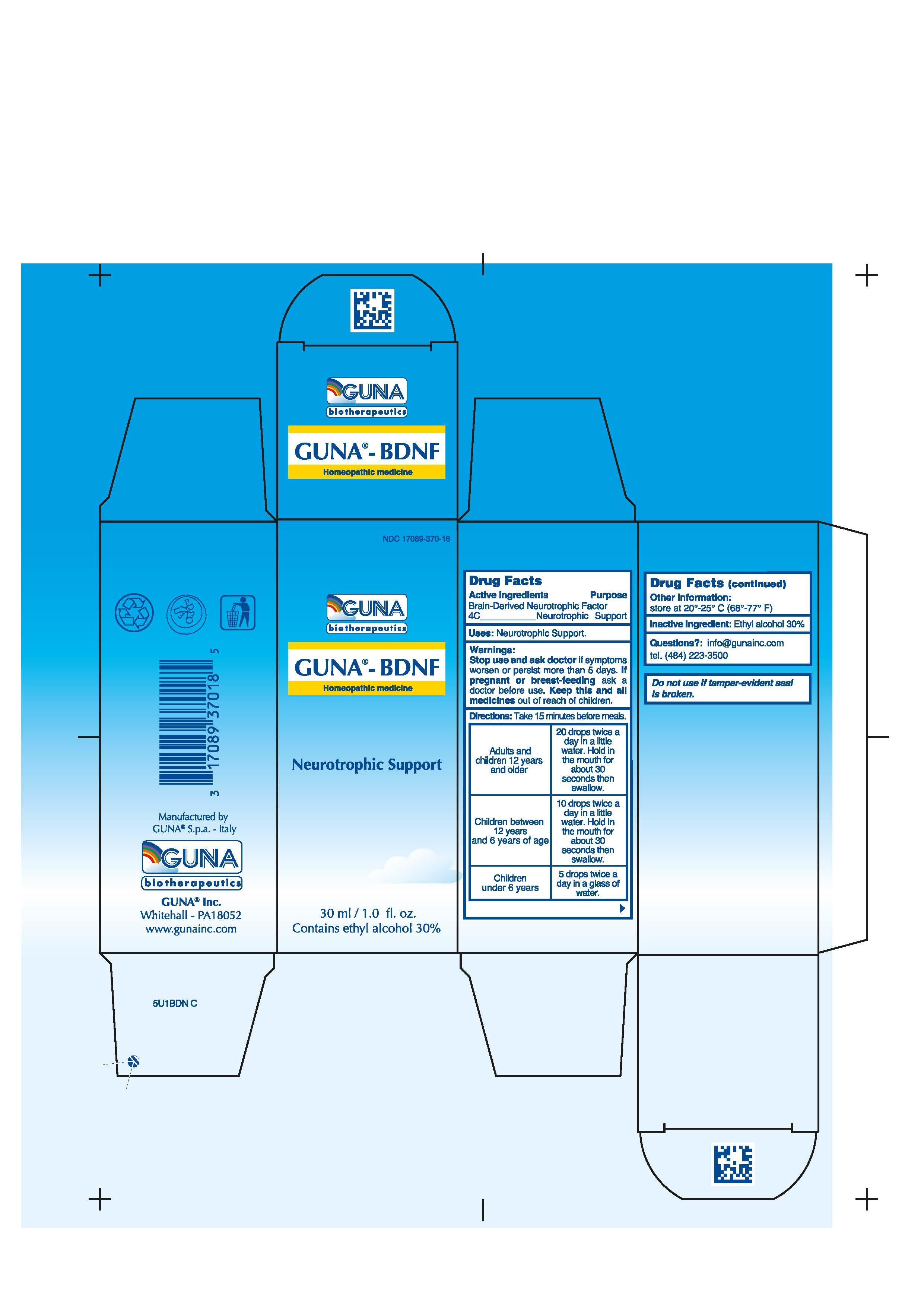 DRUG LABEL: GUNA-BDNF
NDC: 17089-370 | Form: SOLUTION/ DROPS
Manufacturer: Guna spa
Category: homeopathic | Type: HUMAN OTC DRUG LABEL
Date: 20221115

ACTIVE INGREDIENTS: BRAIN-DERIVED NEUROTROPHIC FACTOR HUMAN 4 [hp_C]/30 mL
INACTIVE INGREDIENTS: ALCOHOL 9 mL/30 mL

GUNA-BDNF

ACTIVE INGREDIENT

BRAIN-DERIVED NEUROTROPHIC FACTOR 4C NEUROTROPHIC SUPPORT

PURPOSE

Neurotrophic Support

KEEP OUT OF REACH OF CHILDREN

Keep this and all medicines out of reach of children

INDICATIONS & USAGE

Neurotrophic Support

WARNINGS

- Stop use and ask doctor if symptoms worsen or persist more than 5 days
- If pregnant or breast feeding ask a doctor before use.

DIRECTIONS

Take 15 minutes before meals.
Adults and children 12 years and older 20 drops twice a day in a little water. Hold in the mouth for about 30 seconds then swallow.
Children between 12 years and 6 years of age 10 drops twice a day in a little water. Hold in the mouth for about 30 seconds then swallow.
Children under 6 years 5 drops twice a day in a glass of water.

INACTIVE INGREDIENT

Ethyl Alcohol 30%

INDICATIONS AND USAGE

take 15 minutes before meals

DOSAGE AND ADMINISTRATION

Adults and children twelve years and older: 20 drops twice a day in a little water- Hold in the mouth for about 30 seconds then swallow.

Children between 12 years and 6 years of age: 10 drops twice a day in a little water- Hold in the mouth for about 30 seconds then swallow.

Children under 6 years: 5 drops twice a day in a glass of water.